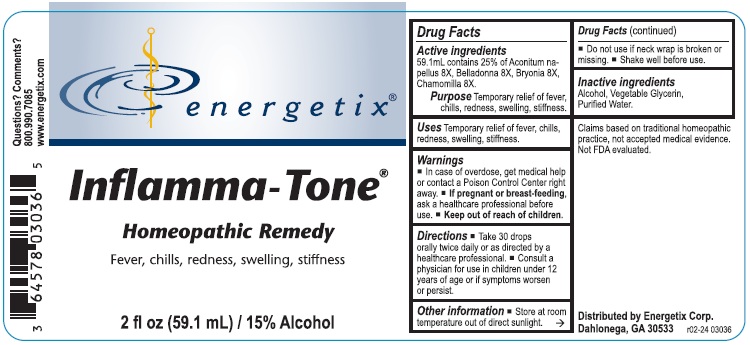 DRUG LABEL: Inflamma-Tone
NDC: 64578-0083 | Form: LIQUID
Manufacturer: Energetix Corporation
Category: homeopathic | Type: HUMAN OTC DRUG LABEL
Date: 20251217

ACTIVE INGREDIENTS: ACONITUM NAPELLUS 8 [hp_X]/1 mL; ATROPA BELLADONNA 8 [hp_X]/1 mL; BRYONIA ALBA ROOT 8 [hp_X]/1 mL; MATRICARIA RECUTITA 8 [hp_X]/1 mL
INACTIVE INGREDIENTS: WATER; GLYCERIN; ALCOHOL

Inflamma-Tone

Active ingredients59.1 mL contains 25% of:

Aconitum Napellus 8X, Belladonna 8X, Bryonia 8X, Chamomilla 8X

Claims based on traditional homepathic practice, not accepted medical evidence.

Not FDA evaluated.

Uses

Temporary relief of fever, chills, redness, swelling, stiffness.

Warnings

- In case of overdose, get medical help or contact a Poison Control Center right away.
- If pregnant or breast-feeding, ask a healthcare professional before use.

• Keep out of reach of children.

Directions

- Take 30 drops orally twice daily or as directed by a healthcare professional.
- Consult a physician for use in children under 12 years of age or if symptoms worsen or persist.

Other information

- Store at room temperature out of direct sunlight.
- Do not use if neck wrap is broken or missing.
- Shake well before use.

Inactive ingredients

Alcohol, Vegetable Glycerin, Purified Water

QUESTIONS

Distributed by
Energetix Corp.
Dahlonega, GA 30533

Questions? Comments?

800.990.7085 www.energetix.com

PACKAGE LABEL

energetix

Inflamma-Tone

Homeopathic Remedy

Fever, chills, redness, swelling, stiffness.

2 fl oz (59.1 mL) / 15% Alcohol

PURPOSE

PurposeTemporary relief of fever, chills, redness, swelling, stiffness.